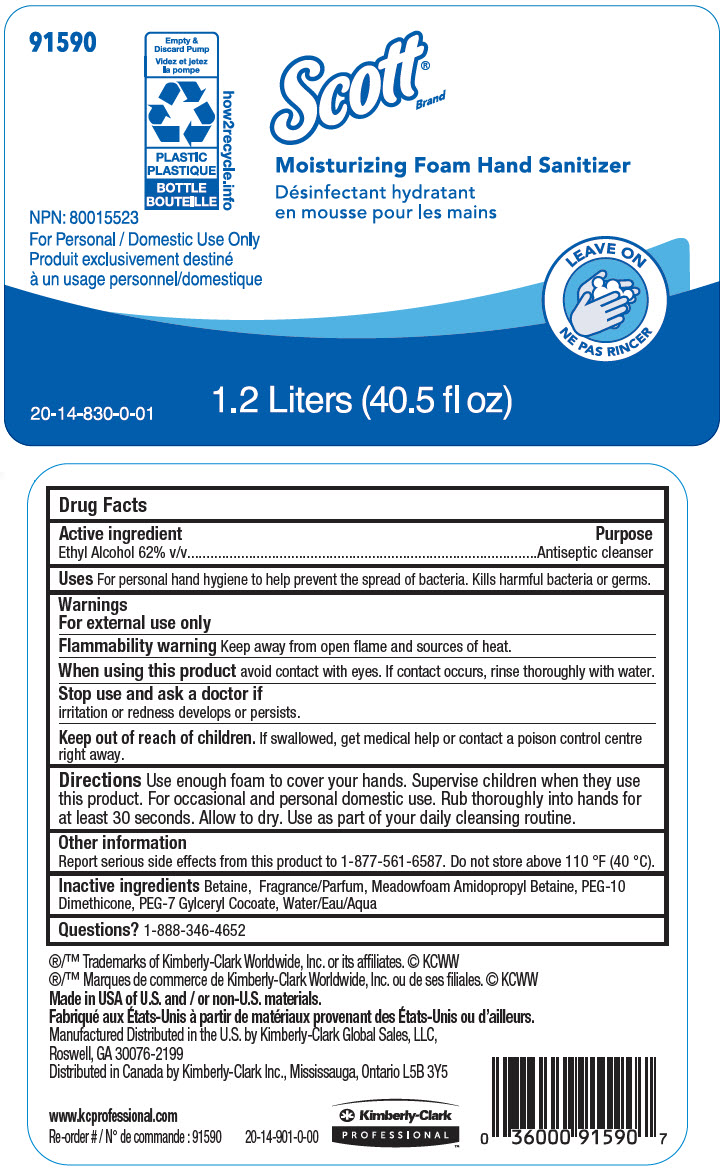 DRUG LABEL: Scott Moisturizing Foam Hand Sanitizer
NDC: 55118-546 | Form: SOLUTION
Manufacturer: Kimberly-Clark
Category: otc | Type: HUMAN OTC DRUG LABEL
Date: 20241212

ACTIVE INGREDIENTS: Alcohol 62 mL/100 mL
INACTIVE INGREDIENTS: Water; Betaine; Meadowfoamamidopropyl Betaine; PEG-7 GLYCERYL COCOATE; PEG-10 DIMETHICONE (600 CST)

Scott® Moisturizing Foam Hand Sanitizer

Drug Facts

Active ingredient

Ethyl Alcohol 62% v/v

Purpose

Antiseptic cleanser

Uses

For personal hand hygiene to help prevent the spread of bacteria. Kills harmful bacteria or germs.

Warnings

For external use only

Flammability warning

Keep away from open flame and sources of heat.

When using this product avoid contact with eyes. If contact occurs, rinse thoroughly with water.

Stop use and ask a doctor if

irritation or redness develops or persists.

Keep out of reach of children. If swallowed, get medical help or contact a poison control centre right away.

Directions

Use enough foam to cover your hands. Supervise children when they use this product. For occasional and personal domestic use. Rub thoroughly into hands for at least 30 seconds. Allow to dry. Use as part of your daily cleansing routine.

Other information

Report serious side effects from this product to 1-877-561-6587. Do not store above 110 °F (40 °C).

Inactive ingredients

Betaine, Fragrance, Meadowfoam Amidopropyl Betaine, PEG-10 Dimethicone, PEG-7 Gylceryl Cocoate, Water

Questions?

1-888-346-4652

Manufactured Distributed in the U.S. by Kimberly-Clark Global Sales, LLC, Roswell, GA 30076-2199
Distributed in Canada by Kimberly-Clark Inc., Mississauga, Ontario L5B 3Y5

PRINCIPAL DISPLAY PANEL - 1.2 Liter Bottle Label

91590

Empty &
Discard Pump

PLASTIC
BOTTLE

how2recycle.info

Scott®
Brand

Moisturizing Foam Hand Sanitizer

NPN: 80015523
For Personal / Domestic Use Only

LEAVE ON

20-14-830-0-01

1.2 Liters (40.5 fl oz)